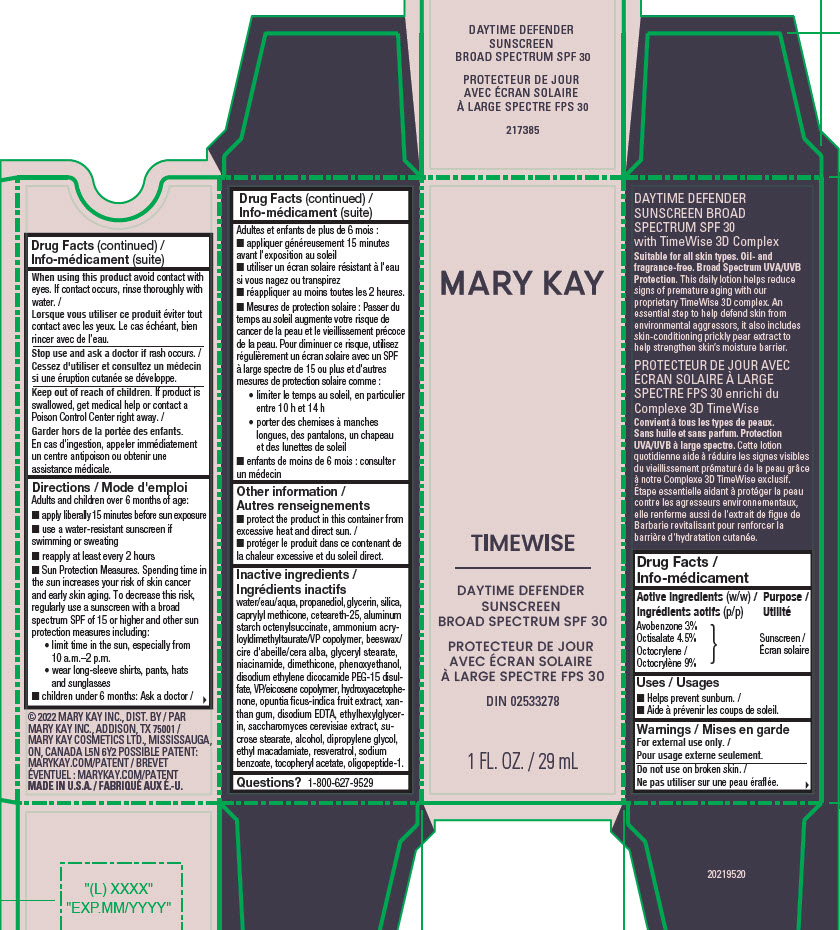 DRUG LABEL: Mary Kay TimeWise Daytime Defender Sunscreen Broad Spectrum SPF 30
NDC: 51531-7385 | Form: LOTION
Manufacturer: Mary Kay Inc.
Category: otc | Type: HUMAN OTC DRUG LABEL
Date: 20241217

ACTIVE INGREDIENTS: OCTISALATE 4.5 g/100 g; OCTOCRYLENE 9 g/100 g; AVOBENZONE 3 g/100 g
INACTIVE INGREDIENTS: GLYCERYL MONOSTEARATE; ALPHA-TOCOPHEROL ACETATE; AMMONIUM ACRYLOYLDIMETHYLTAURATE/VP COPOLYMER; PHENOXYETHANOL; PRICKLY PEAR FRUIT; SODIUM BENZOATE; WATER; ALCOHOL; RESVERATROL; ALUMINUM STARCH OCTENYLSUCCINATE; NIACINAMIDE; SILICON DIOXIDE; CETEARETH-25; GLYCERIN; HYDROXYACETOPHENONE; SUCROSE STEARATE; DIPROPYLENE GLYCOL; EDETATE DISODIUM ANHYDROUS; ETHYLHEXYLGLYCERIN; ETHYL MACADAMIATE; OLIGOPEPTIDE-10; DIMETHICONE; XANTHAN GUM; SACCHAROMYCES CEREVISIAE; DISODIUM ETHYLENE DICOCAMIDE PEG-15 DISULFATE; VINYLPYRROLIDONE/EICOSENE COPOLYMER; YELLOW WAX; PROPANEDIOL; CAPRYLYL TRISILOXANE

Mary Kay TimeWise Daytime Defender Sunscreen Broad Spectrum SPF 30

Active ingredients

Avobenzone 3% (w/w)

Octisalate 4.5% (w/w)

Octocrylene 9% (w/w)

Purpose

Sunscreen

Uses

Helps prevent sunburn.

Warnings

For external use only.

Do not use

on broken skin.

When using this product

avoid contact with eyes. If contact occurs, rinse thoroughly with water.

Stop use and ask a doctor

if rash occurs.

Keep out of reach of children.

If product is swallowed, get medical help or contact a Poison Control Center right away.

Directions

Adults and children over 6 months of age: ■ apply liberally15 minutes before sun exposure ■ use a water-resistant sunscreen if swimming or sweating ■ reapply at least every 2 hours ■ Sun Protection Measures. Spending time in the sun increases your risk of skin cancer and early skin aging. To decrease this risk, regularly use a sunscreen with a broad spectrum SPF of 15 or higher and other sun protection measures including: • limit time in the sun, especially from10 a.m.–2 p.m. • wear long-sleeve shirts, pants, hatsand sunglasses ■ children under 6 months: Ask a doctor

Other information

■ protect the product in this container from excessive heat and direct sun.

Inactive ingredients

water/eau/aqua, propanediol, glycerin, silica, caprylyl methicone, ceteareth-25, aluminum starch octenylsuccinate, ammonium acryloyldimethyltaurate/VP copolymer, beeswax/ cire d'abeille/cera alba, glyceryl stearate, niacinamide, dimethicone, phenoxyethanol, disodium ethylene dicocamide PEG-15 disulfate, VP/eicosene copolymer, hydroxyacetophenone, opuntia ficus-indica fruit extract, xanthan gum, disodium EDTA, ethylhexylglycerin, saccharomyces cerevisiae extract, sucrose stearate, alcohol, dipropylene glycol, ethyl macadamiate, resveratrol, sodium benzoate, tocopheryl acetate, oligopeptide-1.

Questions?

1-800-627-9529

Principal Display Panel - 29 ml carton

Mary Kay

TimeWise

DAYTIME DEFENDER
SUNSCREEN
BROAD SPECTRUM SPF 30

1 FL. OZ. / 29 mL